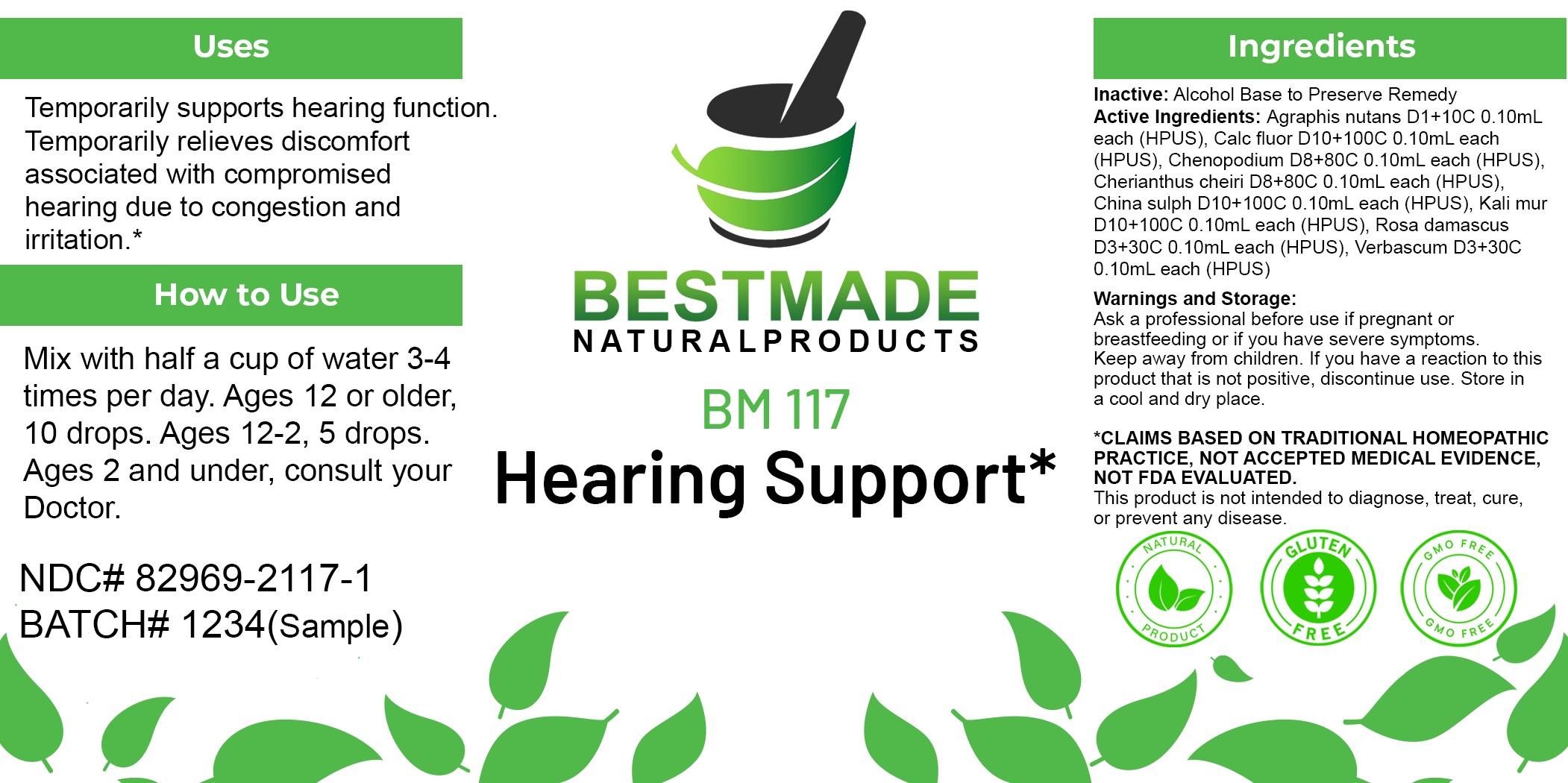 DRUG LABEL: Bestmade Natural Products BM117
NDC: 82969-2117 | Form: LIQUID
Manufacturer: Bestmade Natural Products
Category: homeopathic | Type: HUMAN OTC DRUG LABEL
Date: 20250207

ACTIVE INGREDIENTS: CALCIUM FLUORIDE 30 [hp_C]/30 [hp_C]; ROSA X DAMASCENA FLOWERING TOP 30 [hp_C]/30 [hp_C]; DYSPHANIA AMBROSIOIDES WHOLE 30 [hp_C]/30 [hp_C]; POTASSIUM CHLORIDE 30 [hp_C]/30 [hp_C]; VERBASCUM THAPSUS WHOLE 30 [hp_C]/30 [hp_C]; HYACINTHOIDES NON-SCRIPTA WHOLE 30 [hp_C]/30 [hp_C]; QUININE SULFATE 30 [hp_C]/30 [hp_C]; ERYSIMUM CHEIRI SEED 30 [hp_C]/30 [hp_C]
INACTIVE INGREDIENTS: ALCOHOL 30 [hp_C]/30 [hp_C]

BM117

DOSAGE AND ADMINISTRATION

How to Use

Mix with half a cup of water 3-4 times per day. Ages 12 or older, 10 drops. Ages 12-2, 5 drops. Ages 2 and under, consult your Doctor.

Inactive:

Alcohol Base to Preserve Product

ACTIVE INGREDIENT

Agraphis nutans D1+10C 0.10mL each (HPUS), Calc fluor D10+100C 0.10mL each (HPUS), Chenopodium D8+80C 0.10mL each (HPUS), Cherianthus cheiri D8+80C 0.10mL each (HPUS), China sulph D10+100C 0.10mL each (HPUS), Kali mur D10+100C 0.10mL each (HPUS), Rosa damascus D3+30C 0.10mL each (HPUS), Verbascum D3+30C 0.10mL each (HPUS)

Uses
Temporarily supports hearing function. Temporarily relieves discomfort associated with compromised hearing due to congestion and
irritation.*

Uses
Temporarily supports hearing function. Temporarily relieves discomfort associated with compromised hearing due to congestion and
irritation.*

KEEP OUT OF REACH OF CHILDREN

Warnings and Storage:

Ask a professional before use if pregnant or breastfeeding or if you have severe symptoms.

Keep away from children. If you have a reaction to this product that is not positive, discontinue use. Store in a cool and dry place

*CLAIMS BASED ON TRADITIONAL HOMEOPATHIC PRACTICE, NOT ACCEPTED MEDICAL EVIDENCE NOT FDA EVALUATED.
This product is not intended to diagnose, treat, cure, or prevent any disease.

Warnings and Storage:

Ask a professional before use if pregnant or breastfeeding or if you have severe symptoms.

Keep away from children. If you have a reaction to this product that is not positive, discontinue use. Store in a cool and dry place

*CLAIMS BASED ON TRADITIONAL HOMEOPATHIC PRACTICE, NOT ACCEPTED MEDICAL EVIDENCE NOT FDA EVALUATED.
This product is not intended to diagnose, treat, cure, or prevent any disease.

Entire package label